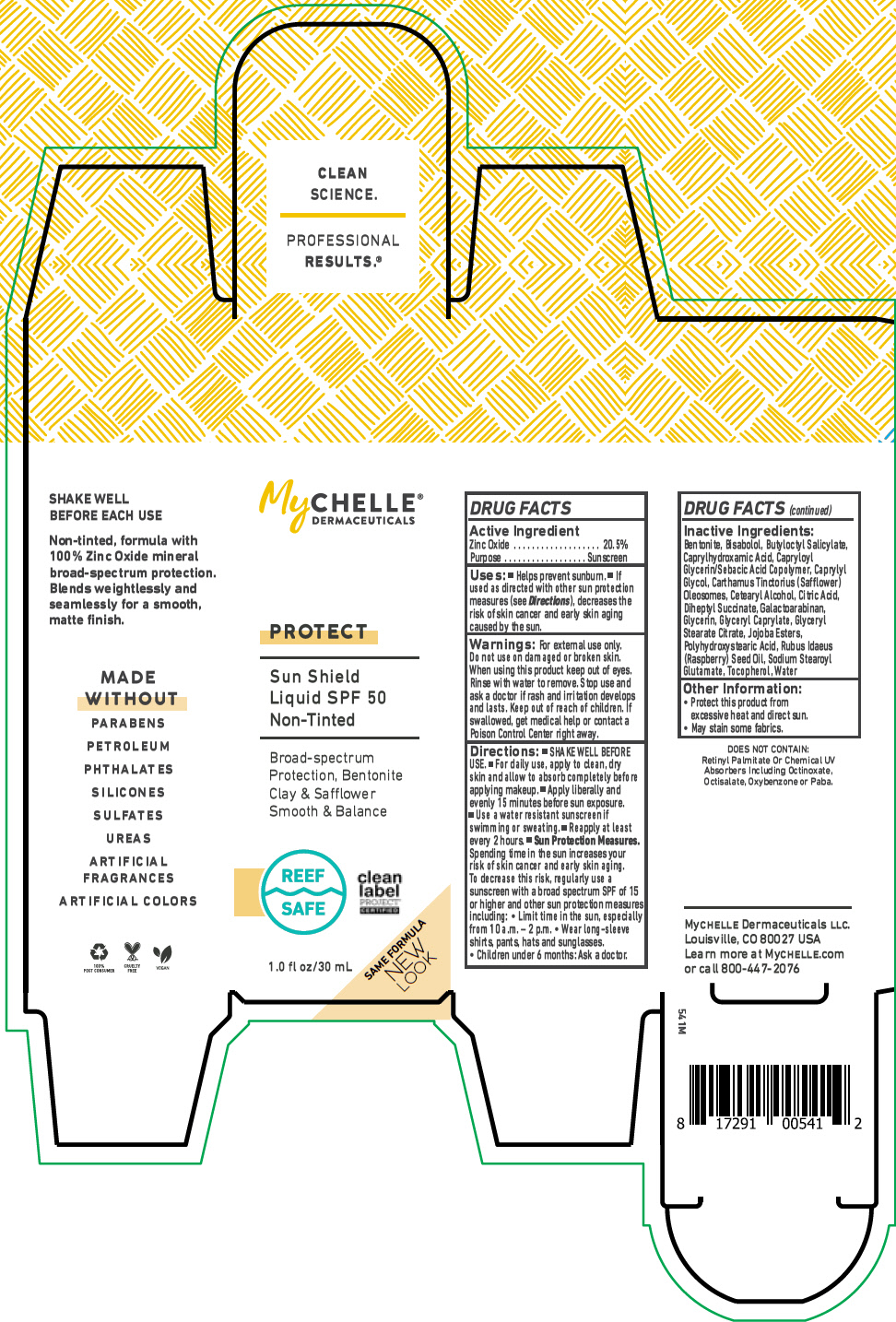 DRUG LABEL: MyChelle Dermaceuticals Sun Shield SPF 50 Non-Tinted 
NDC: 72805-081 | Form: LIQUID
Manufacturer: French Transit, Ltd.
Category: otc | Type: HUMAN OTC DRUG LABEL
Date: 20220107

ACTIVE INGREDIENTS: Zinc Oxide 20.5 g/100 mL
INACTIVE INGREDIENTS: Water; Bentonite; LEVOMENOL; Butyloctyl Salicylate; Caprylhydroxamic Acid; CAPRYLOYL GLYCERIN/SEBACIC ACID COPOLYMER (2000 MPA.S); Caprylyl Glycol; CARTHAMUS TINCTORIUS SEED OLEOSOMES; CETOSTEARYL ALCOHOL; ANHYDROUS CITRIC ACID; Diheptyl Succinate; Galactoarabinan; Glycerin; GLYCERYL MONOCAPRYLATE; Glyceryl Stearate Citrate; HYDROGENATED JOJOBA OIL, RANDOMIZED; POLYHYDROXYSTEARIC ACID (2300 MW); RASPBERRY SEED OIL; Sodium Stearoyl Glutamate; Tocopherol

MyChelle® Dermaceuticals Sun Shield Liquid SPF 50 Non-Tinted
Protect

DRUG FACTS

Active Ingredient

Zinc Oxide 20.5%

Purpose

Sunscreen

Uses

- Helps prevent sunburn.
- If used as directed with other sun protection measures (see Directions), decreases the risk of skin cancer and early skin aging caused by the sun.

Warnings

For external use only. Do not use on damaged or broken skin. When using this product keep out of eyes. Rinse with water to remove. Stop use and ask a doctor if rash and irritation develops and lasts.

Keep out of reach of children. If swallowed, get medical help or contact a Poison Control Center right away.

Directions

- SHAKE WELL BEFORE USE.
- For daily use, apply to clean, dry skin and allow to absorb completely before applying makeup.
- Apply liberally and evenly 15 minutes before sun exposure.
- Use a water resistant sunscreen if swimming or sweating.
- Reapply at least every 2 hours.
- Sun Protection Measures. Spending time in the sun increases your risk of skin cancer and early skin aging. To decrease this risk, regularly use a sunscreen with a broad spectrum SPF of 15 or higher and other sun protection measures including:
  - Limit time in the sun, especially from 10 a.m. – 2 p.m.
  - Wear long-sleeve shirts, pants, hats and sunglasses.
  - Children under 6 months: Ask a doctor.

Inactive Ingredients

Bentonite, Bisabolol, Butyloctyl Salicylate, Caprylhydroxamic Acid, Capryloyl Glycerin/Sebacic Acid Copolymer, Caprylyl Glycol, Carthamus Tinctorius (Safflower) Oleosomes, Cetearyl Alcohol, Citric Acid, Diheptyl Succinate, Galactoarabinan, Glycerin, Glyceryl Caprylate, Glyceryl Stearate Citrate, Jojoba Esters, Polyhydroxystearic Acid, Rubus Idaeus (Raspberry) Seed Oil, Sodium Stearoyl Glutamate, Tocopherol, Water

Other Information

- Protect this product from excessive heat and direct sun.
- May stain some fabrics.

PRINCIPAL DISPLAY PANEL - 30 mL Bottle Box

MyCHELLE®
DERMACEUTICALS

PROTECT

Sun Shield
Liquid SPF 50
Non-Tinted

Broad-spectrum
Protection, Bentonite
Clay & Safflower
Smooth & Balance

REEF
SAFE

clean
label
PROJECT®
CERTIFIED

1.0 fl oz/30 mL

SAME FORMULA
NEW
LOOK